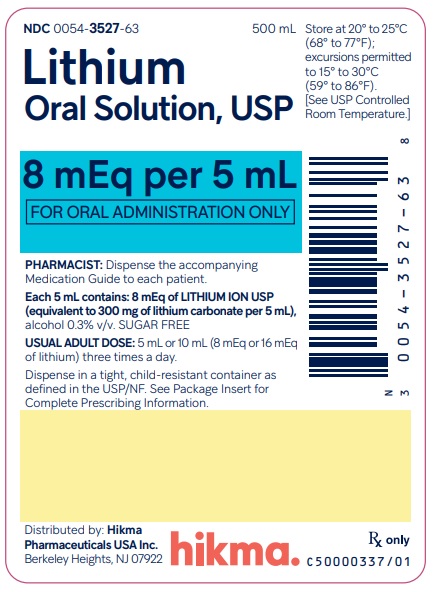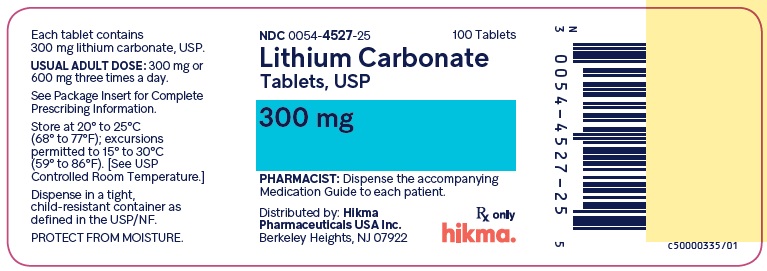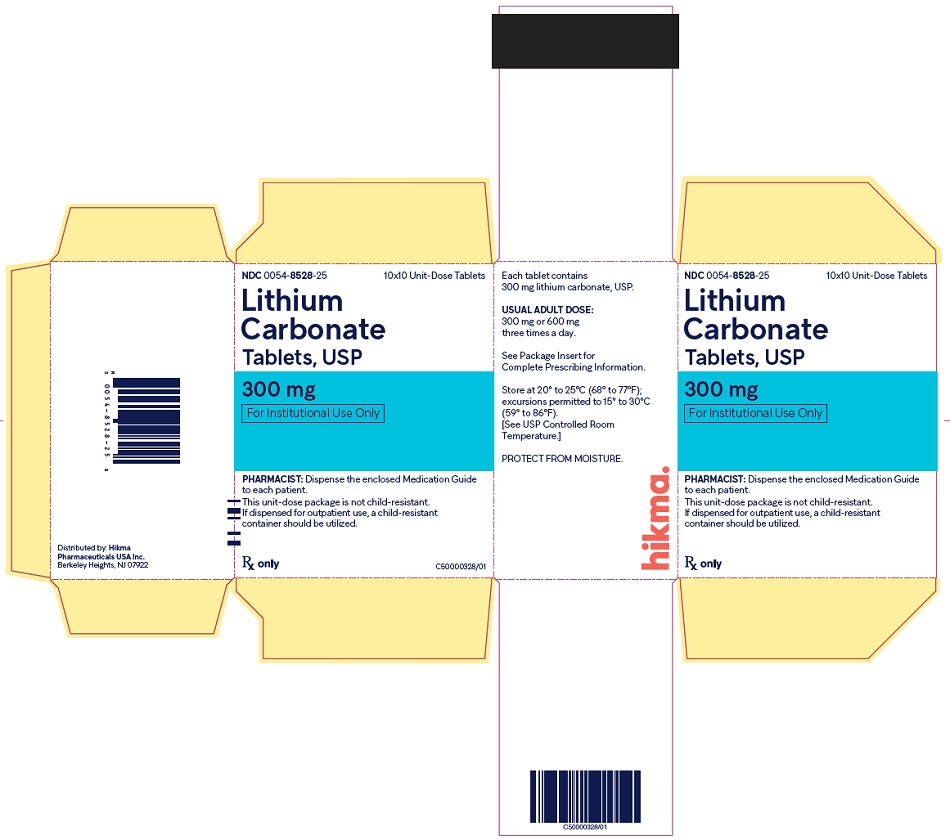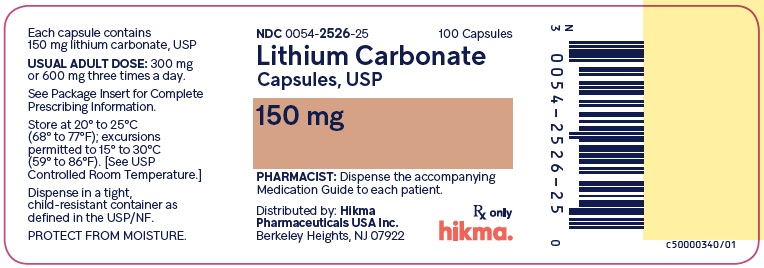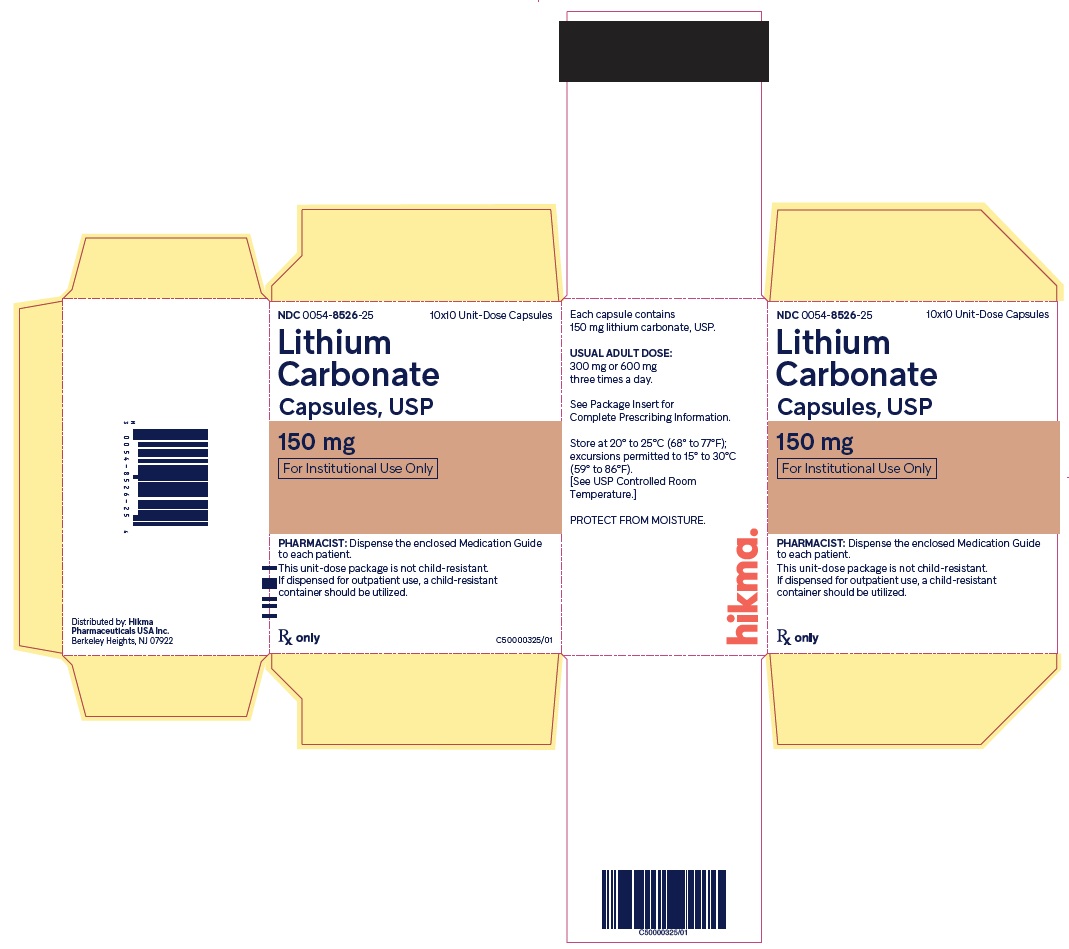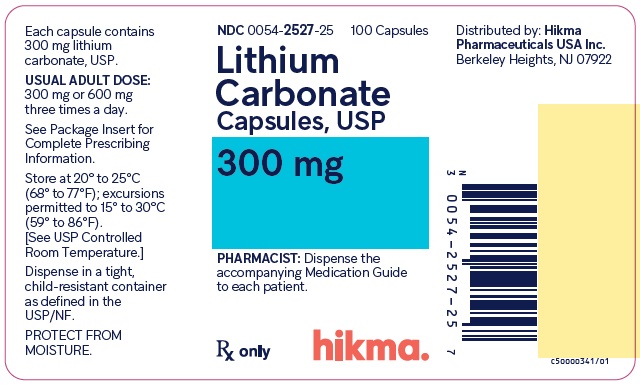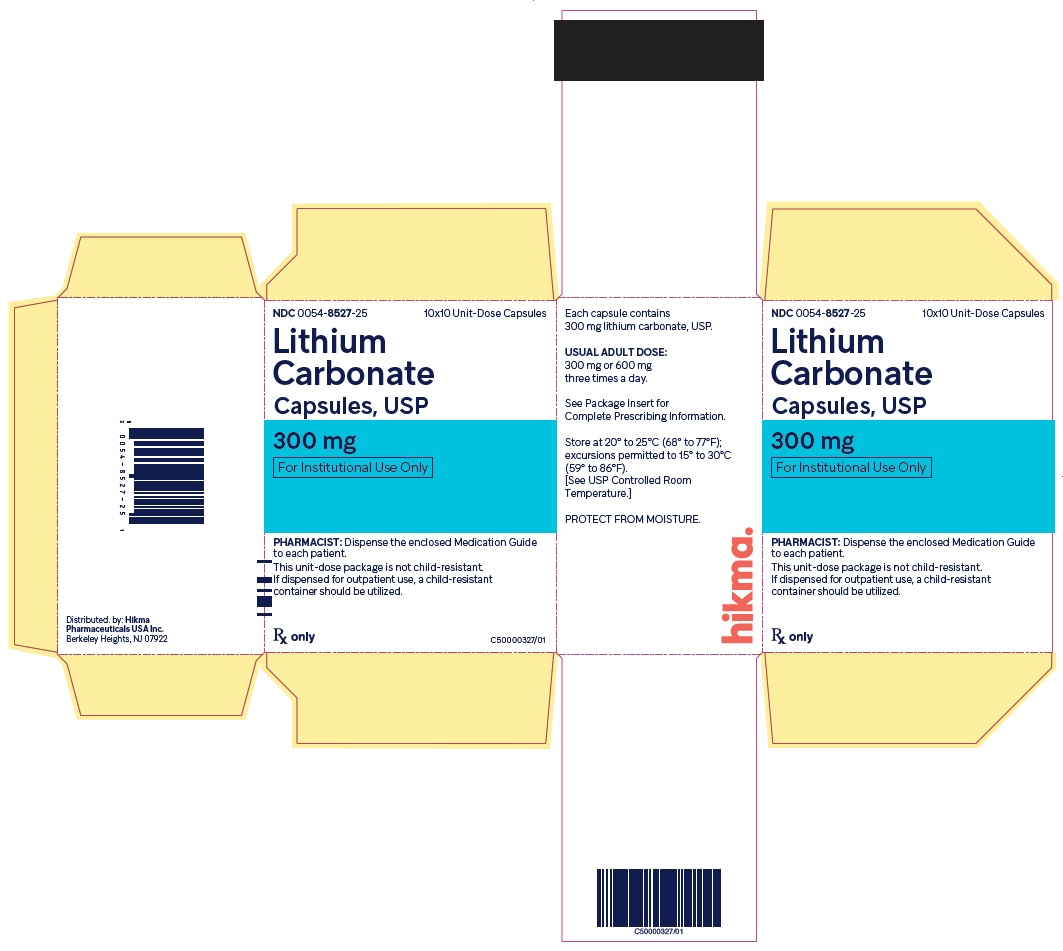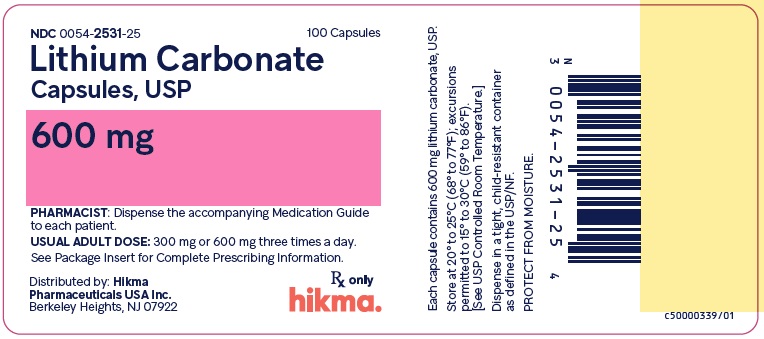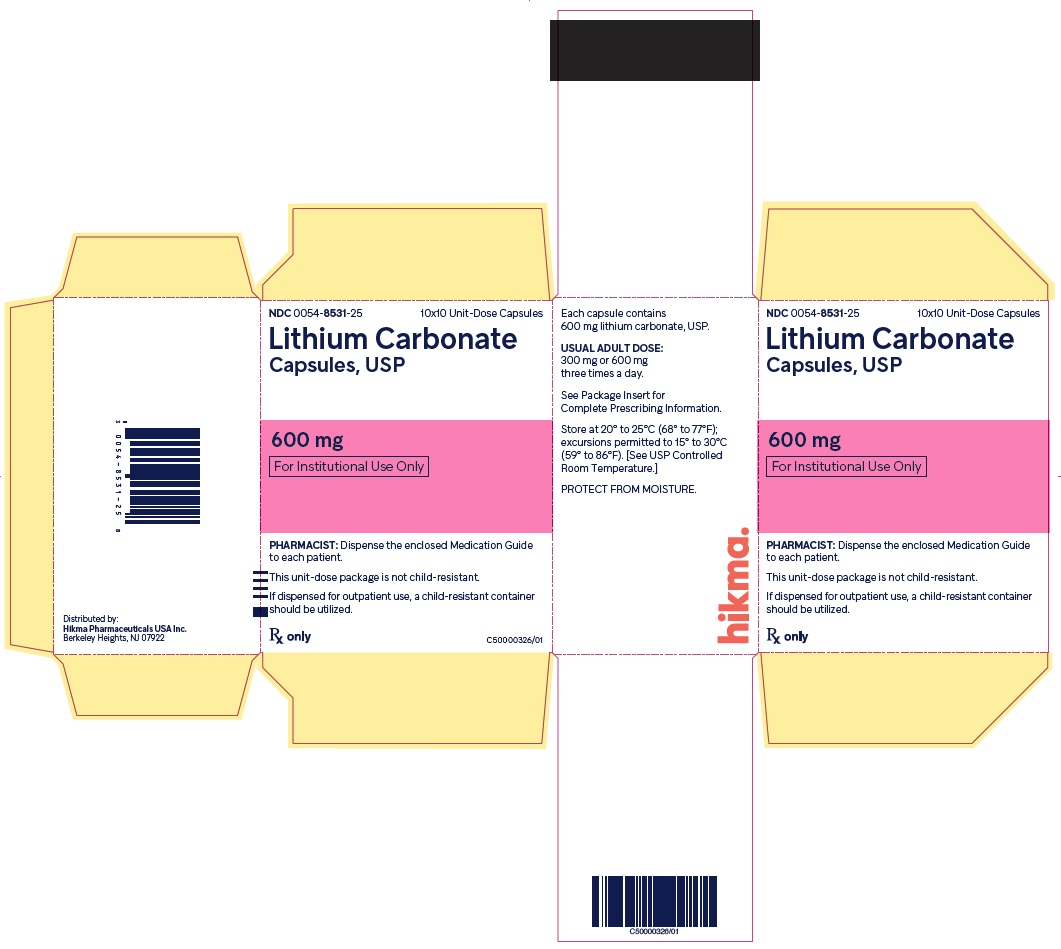 DRUG LABEL: Lithium Carbonate
NDC: 0054-8528 | Form: TABLET
Manufacturer: Hikma Pharmaceuticals USA Inc.
Category: prescription | Type: HUMAN PRESCRIPTION DRUG LABEL
Date: 20221122

ACTIVE INGREDIENTS: LITHIUM CARBONATE 300 mg/1 1
INACTIVE INGREDIENTS: CALCIUM STEARATE; MICROCRYSTALLINE CELLULOSE; POVIDONE K30; SODIUM LAURYL SULFATE; SODIUM STARCH GLYCOLATE TYPE A POTATO; WATER

HIGHLIGHTS OF PRESCRIBING INFORMATION

These highlights do not include all the information needed to use LITHIUM and LITHIUM CARBONATE safely and effectively. See full prescribing information for LITHIUM and LITHIUM CARBONATE.
LITHIUM oral solution, for oral use
LITHIUM CARBONATE tablets, for oral use
LITHIUM CARBONATE capsules, for oral use
Initial U.S. Approval: 1970

WARNING: LITHIUM TOXICITY

See full prescribing information for complete boxed warning.

Lithium toxicity is closely related to serum lithium concentrations, and can occur at doses close to therapeutic concentrations. Facilities for prompt and accurate serum lithium determinations should be available before initiating therapy (2.3, 5.1).

1 INDICATIONS AND USAGE

Lithium is a mood-stabilizing agent indicated as monotherapy for the treatment of bipolar I disorder:

- Treatment of acute manic and mixed episodes in patients 7 years and older (1)
- Maintenance treatment in patients 7 years and older (1)

2 DOSAGE AND ADMINISTRATION

- Recommended starting dosage for adults and pediatric patients over 30 kg (2.2):
  - Tablets or Capsules: 300 mg, three times daily, or
  - Oral Solution: 8mEq lithium (5 mL) three times daily
- Recommended starting dosage for pediatric patients 20 to 30 kg (2.2):
  - Tablets or Capsules: 300 mg twice daily, or
  - Oral Solution: 8mEq (5mL), twice daily
- Obtain serum lithium concentration assay after 3 days, drawn 12 hours after the last oral dose and regularly until patient is stabilized.
- Acute Manic or Mixed Episodes (patients 7 years and older): Titrate to serum lithium concentrations 0.8 to 1.2 mEq/L (2.2).
- Maintenance Treatment for Bipolar I Disorder (patients 7 years and older): Titrate to serum lithium concentrations 0.8 to 1 mEq/L (2.2).
- Pre-treatment Screening: Evaluate renal function, vital signs, electrolytes, thyroid function, concurrent medications, and pregnancy status (2.1).
- Mild to Moderate Renal Impairment (CLer 30 to 89 mL/min): Start with dosages less than those for patients with normal renal function, titrate slowly with frequent monitoring (2.5).
- Severe Renal Impairment (CLer<30mL/min): Avoid use of lithium (2.5).

3 DOSAGE FORMS AND STRENGTHS

- Oral Solution: 8 mEq of lithium (Li^+) per 5mL (3)
- Tablets: 300 mg of lithium carbonate (3)
- Capsules: 150 mg, 300 mg, 600 mg of lithium carbonate (3)

4 CONTRAINDICATIONS

Known hypersensitivity to any inactive ingredient in the drug product. (4)

5 WARNINGS AND PRECAUTIONS

- Lithium-Induced Polyuria: May develop during initiation of treatment. Increases risk of lithium toxicity. Educate patient to avoid dehydration. Monitor for lithium toxicity and metabolic acidosis. Discontinue lithium or treat with amiloride as a therapeutic agent (5.2).
- Hyponatremia: Symptoms are more severe with faster-onset hyponatremia. Dehydration from protracted sweating, diarrhea, or elevated temperatures from infection increases risk of hyponatremia and lithium toxicity. Educate patients on maintaining a normal diet with salt and staying hydrated. Monitor for and treat hyponatremia and lithium toxicity, which may necessitate a temporary reduction or cessation of lithium and infusion of serum sodium (5.3).
- Lithium-Induced Chronic Kidney Disease: Associated with structural changes in patients on chronic lithium therapy. Monitor kidney function during treatment with lithium (5.4).
- Encephalopathic Syndrome: Increased risk in patients treated with lithium and an antipsychotic. Monitor routinely for changes to cognitive function (5.5).
- Hypothyroidism and Hyperthyroidism: Monitor thyroid function regularly (5.7).
- Hypercalcemia and Hyperparathyroidism: Associated with long-term lithium use. Monitor serum calcium (5.8).

6 ADVERSE REACTIONS

Common Adverse Reactions:

- Adult Patients: fine hand tremor, polyuria, mild thirst, nausea, general discomfort during initial treatment (6)
- Pediatric Patients (7-17 years): nausea/vomiting, polyuria, thyroid abnormalities, tremor, thirst/polydipsia, dizziness, rash/dermatitis, ataxia/gait disturbance, decreased appetite, and blurry vision (6)

To report SUSPECTED ADVERSE REACTIONS, contact Hikma Pharmaceuticals USA Inc. at 1-800-962-8364 or FDA at 1-800-FDA-1088 or www.fda.gov/medwatch.

7 DRUG INTERACTIONS

- Diuretics, NSAID, renin-angiotensin system antagonists, or metronidazole may increase lithium serum concentrations. Recommend frequent monitoring of serum lithium concentration and adjust dosage when necessary. (2.3, 7.1)
- Serotonergic Agents: Increased risk of serotonin syndrome when co-administered with lithium. (5.6, 7.1)
- Antipsychotics: There have been reports of neurologic adverse reactions in patients treated with lithium and an antipsychotic, ranging from extrapyramidal symptoms to neuroleptic malignant syndrome. (5.5, 7.1)

8 USE IN SPECIFIC POPULATIONS

- Pregnancy: May cause fetal and/or neonatal harm (8.1)
- Renal Impairment: Use caution during dose selection, starting with dosages less than those for patients with normal renal function while carefully monitoring for side effects (2.5, 6)

FULL PRESCRIBING INFORMATION

WARNING: LITHIUM TOXICITY

Lithium toxicity is closely related to serum lithium concentrations, and can occur at doses close to therapeutic concentrations. Facilities for prompt and accurate serum lithium determinations should be available before initiating treatment [see Dosage and Administration (2.3), Warnings and Precautions (5.1)].

1 INDICATIONS AND USAGE

Lithium is a mood-stabilizing agent indicated as monotherapy for the treatment of bipolar I disorder:

- Treatment of acute manic and mixed episodes in patients 7 years and older [see Clinical Studies (14)]
- Maintenance treatment in patients 7 years and older [see Clinical Studies (14)]

2 DOSAGE AND ADMINISTRATION

2.1 Pre-treatment Screening

Before initiating treatment with lithium, renal function, vital signs, serum electrolytes, and thyroid function should be evaluated. Concurrent medications should be assessed, and if the patient is a woman of childbearing potential, pregnancy status and potential should be considered.

2.2 Recommended Dosage

See Table 1 for dosage recommendations for acute and maintenance treatment of bipolar I disorder in adult and pediatric patients (7 to 17 years).

Obtain serum lithium concentration assay after 3 days, drawn 12 hours after the last oral dose and regularly until patient is stabilized. Fine hand tremor, polyuria, and thirst may occur during initial therapy for the acute manic phase and may persist throughout treatment. Nausea and general discomfort may also appear during the first few days of lithium administration. These adverse reactions may subside with continued treatment, concomitant administration with food, or temporary reduction or cessation of dosage.

Table 1. Lithium Dosing for Bipolar I Disorder
Patient Group | Formulation | Starting Dose | Dose Titration | Acute Goal |  | Maintenance Goal
Patient Group | Formulation | Starting Dose | Dose Titration | Serum Level | Usual Dose | Serum Level | Usual Dose
Adult and Pediatric Patients over 30 kg | Tablets or capsules | 300 mg three times daily | 300 mg every 3 days | 0.8 to 1.2 mEq/L | 600 mg two to three times daily | 0.8 to 1.0 mEq/L | 300 to 600 mg two to three times daily
Adult and Pediatric Patients over 30 kg | Liquid | 8 mEq (5 mL) three times daily | 8 mEq (5 mL) every 3 days | 0.8 to 1.2 mEq/L | 16 mEq (10mL) two to three times daily | 0.8 to 1.0 mEq/L | 8 to 16 mEq (5 to 10 mL) two to three times daily
Pediatric Patients 20 to 30 kg | Tablets or capsules | 300 mg twice daily | 300 mg weekly | 0.8 to 1.2 mEq/L | 600 to 1500 mg in divided doses daily | 0.8 to 1.0 mEq/L | 600 to 1200 mg in divided doses daily
Pediatric Patients 20 to 30 kg | Liquid | 8 mEq (5 mL) twice daily | 8 mEq (5 mL) weekly | 0.8 to 1.2 mEq/L | 16 to 40 mEq (10 to 25 mL) in divided doses daily | 0.8 to 1.0 mEq/L | 16 to 32 mEq (10 to 20 mL) in divided doses daily

Each 5 mL of Lithium Oral Solution contains 8 mEq of lithium ion (Li^+) which is equivalent to the amount of lithium in 300 mg of lithium carbonate. See Table 2 for lithium carbonate and lithium oral solution dose conversion.

Table 2. Lithium Carbonate and Lithium Oral Solution Dose Conversion

Lithium Carbonate Tablets or Capsules | Lithium Oral Solution
150 mg | 4 mEq (2.5 mL)
300 mg | 8 mEq (5 mL)
600 mg | 16 mEq (10 mL)

2.3 Serum Lithium Monitoring

Blood samples for serum lithium determination should be drawn immediately prior to the next dose when lithium concentrations are relatively stable (i.e., 12 hours after the previous dose). Total reliance must not be placed on serum concentrations alone. Accurate patient evaluation requires both clinical and laboratory analysis.

In addition to regular monitoring of serum lithium concentrations for patients on maintenance treatment, serum lithium concentrations should be monitored after any change in dosage, concurrent medication (e.g., diuretics, non-steroidal anti-inflammatory drugs, renin-angiotensin system antagonists, or metronidazole), marked increase or decrease in routinely performed strenuous physical activity (such as an exercise program) and in the event of a concomitant disease [see Boxed Warning, Warnings and Precautions (5.1), Drug Interactions (7.1)].

Patients abnormally sensitive to lithium may exhibit toxic signs at serum concentrations that are within what is considered the therapeutic range. Geriatric patients often respond to reduced dosage, and may exhibit signs of toxicity at serum concentrations ordinarily tolerated by other patients [see Specific Populations (8.5)].

2.4 Dosage Adjustments during Pregnancy and the Postpartum Period

If the decision is made to continue lithium treatment during pregnancy, monitor serum lithium concentrations and adjust the dosage as needed in a pregnant woman because renal lithium clearance increases during pregnancy. Avoid sodium restriction or diuretic administration. To decrease the risk of postpartum lithium intoxication, decrease or discontinue lithium therapy two to three days before the expected delivery date to reduce neonatal concentrations and reduce the risk of maternal lithium intoxication due to the change in vascular volume which occurs during delivery. At delivery, vascular volume rapidly decreases and the renal clearance of lithium may decrease to pre-pregnancy concentrations. Restart treatment at the preconception dose when the patient is medically stable after delivery with careful monitoring of serum lithium concentrations [see Warnings and Precautions (5.1) and Use in Specific Populations (8.1)].

2.5 Dosage Adjustments for Patients with Renal Impairment

Start patients with mild to moderately impaired renal function (creatinine clearance 30 to 89 mL/min evaluated by Cockcroft-Gault) with dosages less than those for patients with normal renal function [see Dosage and Administration (2.2)]. Titrate slowly while frequently monitoring serum lithium concentrations and monitoring for signs of lithium toxicity. Lithium is not recommended for use in patients with severe renal impairment (creatinine clearance less than 30 mL/min evaluated by Cockcroft-Gault) [see Use in Specific Populations (8.6)].

3 DOSAGE FORMS AND STRENGTHS

Each 5 mL of clear, colorless to slightly amber or red lithium oral solution, USP contains 8 mEq lithium ion (Li^+) (equivalent to the amount of lithium in 300 mg of lithium carbonate).

Each 300 mg tablet for oral administration contains: lithium carbonate, USP and is a white to off-white, biconvex tablet, scored on one side with product identification "54 452" debossed on the other side.

Each 150 mg capsule for oral administration contains: lithium carbonate, USP and is an opaque, white capsule, imprinted with product identification “54 213” on both the cap and the body and containing a white powder.

Each 300 mg capsule for oral administration contains: lithium carbonate, USP and is an opaque, light pink-colored capsule, imprinted with product identification “54 463” on both the cap and the body and containing a white powder.

Each 600 mg capsule for oral administration contains: lithium carbonate, USP and is an opaque, light pink-colored cap with white body, imprinted with product identification “54 702” on both the cap and the body and containing a white powder.

4 CONTRAINDICATIONS

Lithium is contraindicated in patients with known hypersensitivity to any inactive ingredient in the lithium carbonate tablet or capsule or lithium citrate products [see Adverse Reactions (6)].

5 WARNINGS AND PRECAUTIONS

5.1 Lithium Toxicity

The toxic concentrations for lithium (≥1.5 mEq/L) are close to the therapeutic range (0.8 to 1.2mEq/L). Some patients abnormally sensitive to lithium may exhibit toxic signs at serum concentrations that are considered within the therapeutic range [see Boxed Warning, Dosage and Administration (2.3)]. Lithium may take up to 24 hours to distribute into brain tissue, so occurrence of acute toxicity symptoms may be delayed.

Neurological signs of lithium toxicity range from mild neurological adverse reactions such as fine tremor, lightheadedness, lack of coordination, and weakness; to moderate manifestations like giddiness, apathy, drowsiness, hyperreflexia, muscle twitching, ataxia, blurred vision, tinnitus, and slurred speech; and severe manifestations such as clonus, confusion, seizure, coma, and death. In rare cases, neurological sequelae may persist despite discontinuing lithium treatment and may be associated with cerebellar atrophy. Cardiac manifestations involve electrocardiographic changes, such as prolonged QT interval, ST and T-wave changes and myocarditis. Renal manifestations include urine concentrating defect, nephrogenic diabetes insipidus, and renal failure. Respiratory manifestations include dyspnea, aspiration pneumonia, and respiratory failure. Gastrointestinal manifestations include nausea, vomiting, diarrhea, and bloating. No specific antidote for lithium poisoning is known [see Overdosage (10)].

The risk of lithium toxicity is increased by:

- Recent onset of concurrent febrile illness
- Concomitant administration of drugs which increase lithium serum concentrations by pharmacokinetic interactions or drugs affecting kidney function [see Drug Interactions (7)].
- Acute ingestion
- Impaired renal function
- Volume depletion or dehydration
- Significant cardiovascular disease
- Changes in electrolyte concentrations (especially sodium and potassium)

Monitor for signs and symptoms of lithium toxicity. If symptoms occur, decrease dosage or discontinue lithium treatment.

5.2 Lithium-Induced Polyuria

Chronic lithium treatment may be associated with diminution of renal concentrating ability, occasionally presenting as nephrogenic diabetes insipidus, with polyuria and polydipsia. The concentrating defect and natriuretic effect characteristic of this condition may develop within weeks of lithium initiation. Lithium can also cause renal tubular acidosis, resulting in hyperchloremic metabolic acidosis. Such patients should be carefully managed to avoid dehydration with resulting lithium retention and toxicity. This condition is usually reversible when lithium is discontinued, although for patients treated with long-term lithium, nephrogenic diabetes insipidus may be only partly reversible upon discontinuation of lithium. Amiloride may be considered as a therapeutic agent for lithium-induced nephrogenic diabetes insipidus.

5.3 Hyponatremia

Lithium can cause hyponatremia by decreasing sodium reabsorption by the renal tubules, leading to sodium depletion. Therefore, it is essential for patients receiving lithium treatment to maintain a normal diet, including salt, and an adequate fluid intake (2500 to 3000 mL) at least during the initial stabilization period. Decreased tolerance to lithium has also been reported to ensue from protracted sweating or diarrhea and, if such occur, supplemental fluid and salt should be administered under careful medical supervision and lithium intake reduced or suspended until the condition is resolved. In addition, concomitant infection with elevated temperatures may also necessitate a temporary reduction or cessation of medication.

Symptoms are also more severe with faster-onset hyponatremia. Mild hyponatremia (i.e., serum Na > 120 mEq/L) can be asymptomatic. Below this threshold, clinical signs are usually present, consisting mainly of changes in mental status, such as altered personality, lethargy, and confusion. For more severe hyponatremia (serum Na < 115 mEq/L), stupor, neuromuscular hyperexcitability, hyperreflexia, seizures, coma, and death can result. During treatment of hyponatremia, serum sodium should not be elevated by more than 10 to 12 mEq/L in 24 hours, or 18 mEq/L in 48 hours. In the case of severe hyponatremia where severe neurologic symptoms are present, a faster infusion rate to correct serum sodium concentration may be needed. Patients rapidly treated or with serum sodium <120mEq/L are more at risk of developing osmotic demyelination syndrome (previously called central pontine myelinolysis). Occurrence is more common among patients with alcoholism, undernutrition, or other chronic debilitating illness. Common signs include flaccid paralysis, dysarthria. In severe cases with extended lesions patients may develop a locked-in syndrome (generalized motor paralysis). Damage often is permanent. If neurologic symptoms start to develop during treatment of hyponatremia, serum sodium correction should be suspended to mitigate the development of permanent neurologic damage.

5.4 Lithium-Induced Chronic Kidney Disease

The predominant form of chronic renal disease associated with long-term lithium treatment is a chronic tubulointerstitial nephropathy (CTIN). The biopsy findings in patients with lithium induced CTIN include tubular atrophy, interstitial fibrosis, sclerotic glomeruli, tubular dilation, and nephron atrophy with cyst formation. The relationship between renal function and morphologic changes and their association with lithium treatment has not been established. CTIN patients might present with nephrotic proteinuria (>3.0g/dL), worsening renal insufficiency and/or nephrogenic diabetes insipidus. Postmarketing cases consistent with nephrotic syndrome in patients with or without CTIN have also been reported. The biopsy findings in patients with nephrotic syndrome include minimal change disease and focal segmental glomerulosclerosis. The discontinuation of lithium in patients with nephrotic syndrome has resulted in remission of nephrotic syndrome.

Kidney function should be assessed prior to and during lithium treatment. Routine urinalysis and other tests may be used to evaluate tubular function (e.g., urine specific gravity or osmolality following a period of water deprivation, or 24-hour urine volume) and glomerular function (e.g., serum creatinine, creatinine clearance, or proteinuria). During lithium treatment, progressive or sudden changes in renal function, even within the normal range, indicate the need for re-evaluation of treatment.

5.5 Encephalopathic Syndrome

An encephalopathic syndrome, characterized by weakness, lethargy, fever, tremulousness and confusion, extrapyramidal symptoms, leukocytosis, elevated serum enzymes, BUN and fasting blood glucose, has occurred in patients treated with lithium and an antipsychotic. In some instances, the syndrome was followed by irreversible brain damage. Because of a possible causal relationship between these events and the concomitant administration of lithium and antipsychotics, patients receiving such combined treatment should be monitored closely for early evidence of neurological toxicity and treatment discontinued promptly if such signs appear. This encephalopathic syndrome may be similar to or the same as neuroleptic malignant syndrome (NMS).

5.6 Serotonin Syndrome

Lithium can precipitate serotonin syndrome, a potentially life-threatening condition. The risk is increased with concomitant use of other serotonergic drugs (including selective serotonin reuptake inhibitors, serotonin and norepinephrine reuptake inhibitors, triptans, tricyclic antidepressants, fentanyl, tramadol, tryptophan, buspirone, and St. John’s Wort) and with drugs that impair metabolism of serotonin, i.e., MAOIs [see Drug Interactions (7.1)].

Serotonin syndrome signs and symptoms may include mental status changes (e.g., agitation, hallucinations, delirium, and coma), autonomic instability (e.g., tachycardia, labile blood pressure, dizziness, diaphoresis, flushing, hyperthermia), neuromuscular symptoms (e.g., tremor, rigidity, myoclonus, hyperreflexia, incoordination), seizures, and gastrointestinal symptoms (e.g., nausea, vomiting, diarrhea).

Monitor all patients taking lithium for the emergence of serotonin syndrome. Discontinue treatment with lithium and any concomitant serotonergic agents immediately if the above symptoms occur, and initiate supportive symptomatic treatment. If concomitant use of lithium with other serotonergic drugs is clinically warranted, inform patients of the increased risk for serotonin syndrome and monitor for symptoms.

5.7 Hypothyroidism or Hyperthyroidism

Lithium is concentrated within the thyroid and can inhibit thyroid synthesis and release which can lead to hypothyroidism. Where hypothyroidism exists, careful monitoring of thyroid function during lithium stabilization and maintenance allows for correction of changing thyroid parameters, if any. Where hypothyroidism occurs during lithium stabilization and maintenance, supplemental thyroid treatment may be used. Paradoxically, some cases of hyperthyroidism have been reported including Grave’s disease, toxic multinodular goiter and silent thyroiditis.

Monitor thyroid function before the initiation of treatment, at three months and every six to twelve months while treatment is ongoing. If serum thyroid tests warrant concern, monitoring should occur more frequently.

5.8 Hypercalcemia and Hyperparathyroidism

Long-term lithium treatment is associated with persistent hyperparathyroidism and hypercalcemia. When clinical manifestations of hypercalcemia are present, lithium withdrawal and change to another mood stabilizer may be necessary. Hypercalcemia may not resolve upon discontinuation of lithium, and may require surgical intervention. Lithium-induced cases of hyperparathyroidism are more often multiglandular compared to standard cases. False hypercalcemia due to plasma volume depletion resulting from nephrogenic diabetes insipidus should be excluded in individuals with mildly increased serum calcium. Monitor serum calcium concentrations regularly.

5.9 Unmasking of Brugada Syndrome

There have been postmarketing reports of a possible association between treatment with lithium and the unmasking of Brugada Syndrome. Brugada Syndrome is a disorder characterized by abnormal electrocardiographic (ECG) findings and a risk of sudden death. Lithium should be avoided in patients with Brugada Syndrome or those suspected of having Brugada Syndrome. Consultation with a cardiologist is recommended if: (1) treatment with lithium is under consideration for patients suspected of having Brugada Syndrome or patients who have risk factors for Brugada Syndrome, e.g., unexplained syncope, a family history of Brugada Syndrome, or a family history of sudden unexplained death before the age of 45 years, (2) patients who develop unexplained syncope or palpitations after starting lithium treatment.

5.10 Pseudotumor Cerebri

Cases of pseudotumor cerebri (increased intracranial pressure and papilledema) have been reported with lithium use. If undetected, this condition may result in enlargement of the blind spot, constriction of visual fields and eventual blindness due to optic atrophy. Consider discontinuing lithium if this syndrome occurs.

6 ADVERSE REACTIONS

The following adverse reactions are described in greater detail in other sections:

- Acute Lithium Toxicity [see Warnings and Precautions (5.1)]
- Lithium-Induced Polyuria [see Warnings and Precautions (5.2)]
- Hyponatremia [see Warnings and Precautions (5.3)]
- Lithium-Induced Chronic Kidney Disease [see Warnings and Precautions (5.4)]
- Encephalopathic Syndrome [see Warnings and Precautions (5.5)]
- Serotonin Syndrome [see Warnings and Precautions (5.6)]
- Hypothyroidism or Hyperthyroidism [see Warnings and Precautions (5.7)]
- Hypercalcemia and Hyperparathyroidism [see Warnings and Precautions (5.8)]
- Unmasking of Brugada Syndrome [see Warnings and Precautions (5.9)]
- Pseudotumor Cerebri [see Warnings and Precautions (5.10)]

6.1 Clinical Trials Experience

Because clinical trials are conducted under widely varying conditions, adverse reaction rates observed in clinical trials of a drug cannot be directly compared to rates in the clinical trials of another drug and may not reflect the rates observed in clinical practice.

Pediatric Patients (7 to 17 years):

Bipolar I Disorder: The following findings are based on an 8-week, placebo-controlled study for acute manic or mixed episodes of bipolar I disorder in pediatric patients 7 to 17 years (N= 81). In this study, lithium was administered at daily doses ranging from 300 to 3600 (mean dose 1483 mg ± 584) with serum levels ranging from 0 to 2.0 (mean level 0.98 mEq/L ± 0.47).

Common Adverse Reactions (incidence ≥ 5% and at least twice the rate of placebo): nausea/vomiting, polyuria, thyroid abnormalities, tremor, thirst/polydipsia, dizziness, rash/dermatitis, ataxia/gait disturbance, decreased appetite, and blurry vision.

Adverse Reactions Occurring at an Incidence of 2% or More in Lithium-Treated Pediatric Patients: Adverse reactions associated with the use of lithium (incidence of 2% or greater, rounded to the nearest percent, and lithium incidence greater than placebo) that occurred during acute therapy (up to 8-weeks in pediatric patients with bipolar disorder) are shown in Table 3.

Table 3: Adverse Reactions Reported in 2% or More of Pediatric Patients on Lithium and That Occurred at Greater Incidence Than in the Placebo Group in the 8-Week Acute Bipolar Trial

System Organ Class/ Preferred Term | Placebo N=28; % | Lithium N=53; %
Gastrointestinal Disorders
Nausea/vomiting | 29 | 57
General Disorders
Fatigue | 4 | 26
Genitourinary Disorders
Polyuria (Including Enuresis) | 14 | 38
Investigations
Increased TSH | 0 | 25
Metabolism and nutrition disorders
Thirst/polydipsia | 11 | 28
Decreased appetite | 4 | 9
Nervous system disorders
Ataxia/gait disturbance | 0 | 13
Blurry vision | 0 | 9
Disorientation | 0 | 6
Dizziness | 7 | 23
Tremor | 7 | 32
Skin and subcutaneous tissue disorders
Rash/dermatitis | 0 | 13

Adult Patients:

The following adverse reactions have been identified following use of lithium. Because these reactions are reported voluntarily from a population of uncertain size, it is not always possible to reliably estimate their frequency or establish a causal relationship to drug exposure.

Central Nervous System: tremor, muscle hyperirritability (fasciculations, twitching, clonic movements of whole limbs), hypertonicity, ataxia, choreoathetotic movements, hyperactive deep tendon reflexes, extrapyramidal symptoms including acute dystonia, cogwheel rigidity, blackout spells, epileptiform seizures, slurred speech, dizziness, vertigo, downbeat nystagmus, incontinence of urine or feces, somnolence, psychomotor retardation, restlessness, confusion, stupor, coma, tongue movements, tics, tinnitus, hallucinations, poor memory, slowed intellectual functioning, startled response, worsening of organic brain syndromes, myasthenic syndromes (rarely).

EEG Changes: diffuse slowing, widening of frequency spectrum, potentiation and disorganization of background rhythm.

Cardiovascular: conduction disturbance (mostly sinus node dysfunction with possibly severe sinus bradycardia and sinoatrial block), ventricular tachyarrhythmia, peripheral vasculopathy (resembling Raynaud’s Syndrome).

ECG Changes: reversible flattening, isoelectricity or rarely inversion of T-waves, prolongation of the QTc interval.

Gastrointestinal: anorexia, nausea, vomiting, diarrhea, gastritis, salivary gland swelling, abdominal pain, excessive salivation, flatulence, indigestion.

Genitourinary: glycosuria, decreased creatinine clearance, albuminuria, oliguria, and symptoms of nephrogenic diabetes insipidus including polyuria, thirst, and polydipsia.

Dermatologic: drying and thinning of hair, alopecia, anesthesia of skin, chronic folliculitis, xerosis cutis, psoriasis onset or exacerbation, generalized pruritus with or without rash, cutaneous ulcers, angioedema, drug reaction with eosinophilia and systemic symptoms (DRESS).

Autonomic Nervous System: blurred vision, dry mouth, impotence/sexual dysfunction.

Miscellaneous: fatigue, lethargy, transient scotoma, exopthalmos, dehydration, weight loss, leukocytosis, headache, transient hyperglycemia, hypermagnesemia, excessive weight gain, edematous swelling of ankles or wrists, dysgeusia/taste distortion (e.g., metallic or salty taste), thirst, swollen lips, tightness in chest, swollen and/or painful joints, fever, polyarthralgia, and dental caries.

7 DRUG INTERACTIONS

7.1 Drugs Having Clinically Important Interactions with Lithium

Table 4: Clinically Important Drug Interactions with Lithium

Diuretics
Clinical Impact: | Diuretic-induced sodium loss may reduce lithium clearance and increase serum lithium concentrations.
Intervention: | More frequent monitoring of serum electrolyte and lithium concentrations. Reduce lithium dosage based on serum lithium concentration and clinical response [see Dosage and Administration (2.3), Warning and Precautions (5.3)].
Non-Steroidal Anti-inflammatory Drugs (NSAID)
Clinical Impact: | NSAID decrease renal blood flow, resulting in decreased renal clearance and increased serum lithium concentrations.
Intervention: | More frequent serum lithium concentration monitoring. Reduce lithium dosage based on serum lithium concentration and clinical response [see Dosage and Administration (2.3)].
Renin-Angiotensin System Antagonists
Clinical Impact: | Concomitant use increase steady-state serum lithium concentrations.
Intervention: | More frequent monitoring of serum lithium concentration. Reduce lithium dosage based on serum lithium concentration and clinical response [see Dosage and Administration (2.3)].
Serotonergic Drugs
Clinical Impact: | Concomitant use can precipitate serotonin syndrome.
Intervention: | Monitor patients for signs and symptoms of serotonin syndrome, particularly during lithium initiation. If serotonin syndrome occurs, consider discontinuation of lithium and/or concomitant serotonergic drugs [see Warnings and Precautions (5.6)].
Nitroimidazole Antibiotics
Clinical Impact: | Concomitant use may increase serum lithium concentrations due to reduced renal clearance.
Intervention: | More frequent monitoring of serum lithium concentration. Reduce lithium dosage based on serum lithium concentration and clinical response [see Dosage and Administration (2.3)].
Acetazolamide, Urea, Xanthine Preparations, Alkalinizing Agents
Clinical Impact: | Concomitant use can lower serum lithium concentrations by increasing urinary lithium excretion.
Intervention: | More frequent serum lithium concentration monitoring. Increase lithium dosage based on serum lithium concentration and clinical response [see Dosage and Administration (2.3)].
Methyldopa, Phenytoin and Carbamazepine
Clinical Impact: | Concomitant use may increase risk of adverse reactions of these drugs.
Intervention: | Monitor patients closely for adverse reactions of methyldopa, phenytoin, and carbamazepine.
Iodide Preparations
Clinical Impact: | Concomitant use may produce hypothyroidism.
Intervention: | Monitor patients for signs or symptoms of hypothyroidism [see Warnings and Precautions (5.7)].
Calcium Channel Blocking Agents (CCB)
Clinical Impact: | Concomitant use may increase the risk of neurologic adverse reactions in the form of ataxia, tremors, nausea, vomiting, diarrhea and/or tinnitus.
Intervention: | Monitor for neurologic adverse reactions.
Atypical and Typical Antipsychotic Drugs
Clinical Impact: | Reports of neurotoxic reactions in patients treated with both lithium and an antipsychotic, ranging from extrapyramidal symptoms to neuroleptic malignant syndrome, as well as reports of an encephalopathic syndrome in few patients treated with concomitant therapy [see Warnings and Precautions (5.5)].
Intervention: | Monitor for neurologic adverse reactions.
Sodium-Glucose Cotransporter 2 (SGLT2) inhibitor
Clinical Impact: | Concomitant use of lithium with an SGLT2 inhibitor may decrease serum lithium concentrations.
Intervention: | Monitor serum lithium concentration more frequently during SGLT2 inhibitor initiation and dosage changes.
Neuromuscular Blocking Agents
Clinical Impact: | Lithium may prolong the effects of neuromuscular blocking agents.
Intervention: | Monitor for prolonged paralysis.

8 USE IN SPECIFIC POPULATIONS

8.1 Pregnancy

Risk Summary:

Lithium may cause harm when administered to a pregnant woman. Early voluntary reports to international birth registries suggested an increase in cardiovascular malformations, especially for Ebstein’s anomaly, with first trimester use of lithium. Subsequent case-control and cohort studies indicate that the increased risk for cardiac malformations is likely to be small; however, the data are insufficient to establish a drug-associated risk. There are concerns for maternal and/or neonatal lithium toxicity during late pregnancy and the postpartum period [see Clinical Considerations]. Published animal developmental and toxicity studies in mice and rats report an increased incidence of fetal mortality, decreased fetal weight, increased fetal skeletal abnormalities, and cleft palate (mouse fetuses only) with oral doses of lithium that produced serum concentrations similar to the human therapeutic range. Other published animal studies report adverse effects on embryonic implantation in rats after lithium administration. Advise pregnant women of the potential risk to a fetus.

The background risk of major birth defects and miscarriage for the indicated population(s) is unknown. In the U.S. general population, the estimated background risk of major birth defects and miscarriage in clinically recognized pregnancies is 2 to 4% and 15 to 20%, respectively.

Clinical Considerations:

Dose Adjustments During Pregnancy and the Postpartum Period: If the decision is made to continue lithium treatment during pregnancy, serum lithium concentrations should be monitored and the dosage adjusted during pregnancy. Two to three days prior to delivery, lithium dosage should be decreased or discontinued to reduce the risk of maternal and/or neonatal toxicity. Lithium may be restarted in the post-partum period at preconception doses in medically stable patients as long as serum lithium levels are closely monitored [see Dosage and Administration (2.4), Warnings and Precautions (5.1)].

Fetal/Neonatal Adverse Reactions: Lithium toxicity may occur in neonates who were exposed to lithium in late pregnancy. A floppy baby syndrome including neurological, cardiac, and hepatic abnormalities that are similar to those seen with lithium toxicity in adults have been observed. Symptoms include hypotonia, respiratory distress syndrome, cyanosis, lethargy, feeding difficulties, depressed neonatal reflexes, neonatal depression, apnea, and bradycardia. Monitor neonates and provide supportive care until lithium is excreted and toxic signs disappear, which may take up to 14 days.

Consider fetal echocardiography between 16 and 20 weeks gestation in a woman with first trimester lithium exposure because of the potential increased risk of cardiac malformations.

8.2 Lactation

Risk Summary:

Limited published data reports the presence of lithium carbonate in human milk with breast milk levels measured at 0.12 to 0.7 mEq or 40 to 45% of maternal plasma levels. Infants exposed to lithium during breastfeeding may have plasma levels that are 30 to 40% of maternal plasma levels. Signs and symptoms of lithium toxicity such as hypertonia, hypothermia, cyanosis, and ECG changes have been reported in some breastfed neonates and infants. Increased prolactin levels have been measured in lactating women, but the effects on milk production are not known. Breastfeeding is not recommended with maternal lithium use; however, if a woman chooses to breastfeed, the infant should be closely monitored for signs of lithium toxicity. Discontinue breastfeeding if a breastfed infant develops lithium toxicity.

Clinical Considerations:

Consider regular monitoring of lithium levels and thyroid function in a breastfed infant.

8.4 Pediatric Use

The safety and effectiveness of lithium for monotherapy treatment of acute manic or mixed episodes of bipolar I disorder and maintenance monotherapy of bipolar I disorder in pediatric patients ages 7 to 17 years of age have been established in an acute-phase clinical trial of 8 weeks in duration followed by a 28-week randomized withdrawal phase [see Dosage and Administration (2.1), Adverse Reactions (6.1), Clinical Pharmacology (12.3), Clinical Studies (14)].

The safety and effectiveness of lithium has not been established in pediatric patients less than 7 years of age with bipolar I disorder.

8.5 Geriatric Use

Clinical studies of lithium carbonate tablets did not include sufficient numbers of subjects aged 65 and over to determine whether they respond differently from younger subjects. Other reported clinical experience has not identified differences in response between the elderly and younger patients. In general, dose selection for an elderly patient should be cautious, usually starting at the low end of the dosing range, reflecting the greater frequency of decreased hepatic, renal, or cardiac function, and of concomitant disease or other treatment.

Lithium is known to be substantially excreted by the kidneys, and the risk of toxic reactions to this drug may be greater in patients with impaired renal function. Because elderly patients are more likely to have decreased renal function, care should be taken in dose selection, and it may be useful to monitor renal function.

8.6 Renal Impairment

As lithium is eliminated primarily through the kidney, lithium renal clearance is decreased in patients with abnormal renal function, and the risk of lithium intoxication increases considerably in this setting. Lithium should not be used in severe renal insufficiency (creatinine clearance less than 30 mL/min evaluated by Cockcroft-Gault), especially if the condition requires adherence to a low-sodium diet [see Dosage and Administration (2.5)].

Start patients with mild to moderately impaired renal function (creatinine clearance 30 to 89 mL/min evaluated by Cockcroft-Gault) with lower doses of lithium and titrate slowly while frequently monitoring serum lithium concentrations and for signs of lithium toxicity [see Dosage and Administration (2.5)].

10 OVERDOSAGE

The toxic concentrations for lithium (≥ 1.5 mEq/L) are close to the therapeutic concentrations [see Warnings and Precautions (5.1)]. At lithium concentrations greater than 3 mEq/L, patients may progress to seizures, coma, and irreversible brain damage.

Treatment:

For current information on the management of poisoning or overdosage, contact the National Poison Control Center at 1-800-222-1222 or www.poison.org.

No specific antidote for lithium poisoning is known. Mild symptoms of lithium toxicity can usually be treated by reduction in dose or cessation of the drug.

In severe cases of lithium poisoning, the goal of treatment is elimination of this ion from the patient. Administration of gastric lavage should be performed, but use of activated charcoal is not recommended as it does not significantly absorb lithium ions. Hemodialysis is the treatment of choice as it is an effective and rapid means of removing lithium in patients with severe toxicity. As an alternative option, urea, mannitol and aminophylline can induce a significant increase in lithium excretion. Appropriate supportive care for the patient should be undertaken. Patients with impaired consciousness should have their airway protected and it is critical to correct any volume depletion or electrolyte imbalance. Patients should be monitored to prevent hypernatremia while receiving normal saline and careful regulation of kidney function is of utmost importance.

Serum lithium concentrations should be closely monitored as there may be a rebound in serum lithium concentrations as a result of delayed diffusion from the body tissues. Likewise, during the late recovery phase, lithium should be re-administered with caution taking into account the possible release of significant lithium stores in body tissues.

11 DESCRIPTION

Each tablet for oral administration contains lithium carbonate USP, 300 mg and the following inactive ingredients: calcium stearate, microcrystalline cellulose, povidone, purified water, sodium lauryl sulfate, and sodium starch glycolate.

Each capsule for oral administration contains lithium carbonate USP, 150 mg, 300 mg or 600 mg and the following inactive ingredient: talc. The capsule shells contain black monogramming ink, FD&C Red No. 40 (300 mg and 600 mg only), gelatin and titanium dioxide. The black monogramming ink contains ammonium hydroxide, ethanol, iron oxide black, isopropyl alcohol, N-butyl alcohol, propylene glycol and shellac glaze.

Each 5 mL of solution for oral administration contains lithium ion (Li^+), 8 mEq (equivalent to amount of lithium in 300 mg of lithium carbonate), alcohol 0.3% v/v and the following other inactive ingredients: citric acid, purified water, raspberry blend, sodium benzoate and sorbitol solution.

Lithium Oral Solution is a palatable oral dosage form of lithium ion. It is prepared in solution from lithium hydroxide and citric acid in a ratio approximately di-lithium citrate.

Lithium is an element of the alkali-metal group with atomic number 3, atomic weight 6.94, and an emission line at 671 nm on the flame photometer.

The empirical formula for Lithium Citrate is C6H5Li3O7; molecular weight 209.93. Lithium acts as an antimanic.

Lithium Carbonate, USP is a granular, white powder with molecular formula Li2CO3 and molecular weight 73.89.

12 CLINICAL PHARMACOLOGY

12.1 Mechanism of Action

The mechanism of action of lithium as a mood stabilizing agent is unknown.

12.3 Pharmacokinetics

Absorption: After oral administration, lithium is reported to be completely absorbed in the upper gastrointestinal tract. Peak serum concentrations (Tmax) occur 0.25 to 3 hours after oral administration of immediate release preparations and 2 to 6 hours after sustained-release preparations.

Distribution: The distribution space of lithium approximates that of total body water, and the plasma protein binding is negligible. After equilibrium, the apparent volume of distribution is 0.7 to 1 L/kg.

Metabolism: Lithium is not metabolized.

Excretion: Lithium is primarily excreted in urine, proportionally to its serum concentration. Lithium is filtered by the glomerulus, and 80% is reabsorbed by passive diffusion in the proximal tubule. The elimination half-life of lithium is approximately 18 to 36 hours. Lithium excretion in feces is insignificant.

Specific Populations:

Pediatric Use: A pharmacokinetic study of lithium was performed in 39 subjects with bipolar I disorder. Both apparent clearance and apparent volume of distribution increase as body weight increases. A lower dose in patients < 30 kg is necessary to achieve lithium exposures in pediatric patients similar to those observed in adults treated at recommended doses of lithium [see Dosage and Administration (2.2)]. The estimated plasma clearance was 0.59 L/h, 0.79 L/h and 1.17 L/h for pediatric patients weighing 20 kg, 30 kg and 50 kg, respectively.

13 NONCLINICAL TOXICOLOGY

13.1 Carcinogenesis, Mutagenesis, Impairment of Fertility

Carcinogenesis: There have been no long-term studies performed in animals to evaluate the carcinogenic potential of lithium.

Mutagenesis: There have been no adequate studies conducted to evaluate the mutagenic and genotoxic potential of lithium.

Impairment of Fertility: There have been no adequate studies performed in animals at current standards to evaluate the effect of lithium treatment on fertility. However, published studies in male mice and rats administered repeated daily dosing of lithium carbonate report adverse effects on male reproductive organs, decreased spermatogenesis and decreased testosterone levels.

14 CLINICAL STUDIES

The safety and efficacy of lithium as a treatment for acute manic or mixed episodes of bipolar I disorder in pediatric patients (ages 7 to ≤18 years) was demonstrated in an 8-week, randomized, placebo-controlled, parallel group study (NCT01166425). In this study, 81 patients with a Young Mania Rating Scale (YMRS) score of 20 or more were randomized to receive lithium or placebo in a 2:1 ratio. Patients weighing more than 30 kg started lithium at 300 mg three times daily (900 mg/day) and could increase their dose by 300 mg every 3 days. Patients weighing 20 to 30 kg started lithium at 300 mg twice daily (600 mg/day) and could increase their dose by 300 mg weekly. No patients weighing less than 20 kg were enrolled. Lithium (mean serum level 0.98 ± 0.47 mEq/L) was statistically significantly superior to placebo in decreasing acute mania or mixed states as measured by the YMRS (see Table 5).

In a 28-week randomized withdrawal analysis, 31 pediatric patients stabilized on lithium were assigned to either continue lithium or switch to placebo. The group receiving lithium demonstrated superiority to those receiving placebo in all-cause discontinuation (see Table 5).

Table 5: Primary Efficacy Results

Analysis | Treatment Group | Change From Baseline at Week 8 in YMRS Summary Score
Analysis | Treatment Group | N | Mean Baseline Score (SD) | LS Mean Change from Baseline (SE) | Difference [Difference (drug minus placebo) in least-squares mean change from baseline.] (95% CI)
Acute Efficacy | Lithium: | 53 | 29.5 (5.6) | -12.9 (3.1) | -5.5 (-10.5, -0.5)
Acute Efficacy | Placebo: | 28 | 30.0 (6.0) | -7.3 (3.1) | -5.5 (-10.5, -0.5)
Analysis | Treatment Group [Patients analyzed by received treatment.] | All-cause Discontinuation
Analysis | Treatment Group [Patients analyzed by received treatment.] | N |  | Number of Discontinued Subjects | Hazard Ratio [Lithium to placebo.]; (95% CI)
Randomized Withdrawal | Lithium: | 17 |  | 7 (41.2%) | 0.28 (0.10, 0.78)
Randomized Withdrawal | Placebo: | 14 |  | 11 (78.6%) | 0.28 (0.10, 0.78)
SD: standard deviation; SE: standard error; LS Mean: least-squares mean; CI: confidence interval.

16 HOW SUPPLIED/STORAGE AND HANDLING

Lithium Oral Solution USP, 8 mEq per 5 mL.

Lithium Oral Solution, USP is supplied as a clear, colorless to slightly amber or red solution.

NDC 0054-3527-63: Bottle of 500 mL

Store and Dispense

Store at 20°C to 25°C (68°F to 77°F); excursions permitted to 15°C to 30°C (59°F to 86°F). [See USP Controlled Room Temperature.] Dispense in a tight, child-resistant container as defined in the USP/NF.

Lithium Carbonate Tablets, USP

300 mg supplied as white to off-white, biconvex tablet, scored on one side with product identification “54 452” debossed on the other side.

NDC 0054-8528-25: 10x10 Unit-Dose
(For Institutional Use Only)

NDC 0054-4527-25: Bottle of 100 Tablets

NDC 0054-4527-31: Bottle of 1,000 Tablets

Lithium Carbonate Capsules, USP

150 mg supplied as opaque white capsules imprinted with product identification “54 213” on both caps and bodies and containing a white powder.

NDC 0054-8526-25: 10x10 Unit-Dose
(For Institutional Use Only).

NDC 0054-2526-25: Bottle of 100 Capsules

300 mg supplied as opaque, light pink-colored capsules imprinted with product identification “54 463” on both caps and bodies and containing a white powder.

NDC 0054-8527-25: 10x10 Unit-Dose
(For Institutional Use Only).

NDC 0054-2527-25: Bottle of 100 Capsules

NDC 0054-2527-31: Bottle of 1,000 Capsules

600 mg supplied as gelatin capsules having opaque, light pink-colored caps with white bodies, imprinted with product identification “54 702” on both caps and bodies and containing a white powder.

NDC 0054-8531-25: 10x10 Unit-Dose
(For Institutional Use Only).

NDC 0054-2531-25: Bottle of 100 Capsules

Storage

Store at 20°C to 25°C (68°F to 77°F); excursions permitted to 15°C to 30°C (59°F to 86°F). [See USP Controlled Room Temperature.] Dispense in a tight, child-resistant container as defined in the USP/NF. PROTECT FROM MOISTURE.

17 PATIENT COUNSELING INFORMATION

Advise the patient to read FDA-approved patient labeling (Medication Guide).

Dosage and Administration:

Advise patients that lithium is a mood stabilizer, and should only be taken as directed. Emphasize the importance of compliance with the prescribed treatment and to not adjust the dose of lithium without first consulting their healthcare provider. Inform patients that they will need to have regular blood draws to determine if their dose of lithium is appropriate.

Instruct patients not to double the dose if a dose is missed, due to the complexity of individualized dosing and potential for lithium toxicity [see Dosage and Administration (2), Warnings and Precautions (5.1)].

Lithium Toxicity:

Inform patients on adverse reactions related to lithium toxicity that require medical attention. Advise patients to discontinue lithium treatment and contact their healthcare provider if clinical signs of lithium toxicity such as diarrhea, vomiting, tremor, lack of muscle coordination, drowsiness, abnormal heart rhythm or muscular weakness occur [see Warnings and Precautions (5.1)].

Lithium-Induced Polyuria:

Counsel patients on the adverse reactions related to lithium-induced polyuria, when to seek medical attention, and the importance of maintaining normal diet with salt and staying hydrated [see Warnings and Precautions (5.2)].

Hyponatremia:

Counsel patients on the adverse reactions of hyponatremia, when to seek medical attention, the importance of maintaining a normal diet including adequate salt intake and staying hydrated [see Warnings and Precautions (5.3)]. Salt supplements and additional fluids may be required if excessive losses occur.

Serotonin Syndrome:

Caution patients about the risk of serotonin syndrome, particularly with the concomitant use of lithium with other serotonergic drugs including SSRIs, SNRIs, triptans, tricyclic antidepressants, fentanyl, tramadol, tryptophan, buspirone, St. John’s Wort, and with drugs that impair metabolism of serotonin (in particular, MAOIs, both those intended to treat psychiatric disorders and also others, such as linezolid) [see Warnings and Precautions (5.6) and Drug Interactions (7)].

Drug Interactions:

Advise patients that many drugs can interact with lithium and to inform their doctor and pharmacist if they are taking any over the counter medication, including herbal medication, or are started on a new prescription [see Drug Interactions (7)].

Somnolence:

Tell patients that lithium may cause somnolence particularly when initiating treatment and to be cautious about operating vehicles or hazardous machinery, until they are reasonably certain that lithium treatment does not affect them adversely [see Adverse Reactions (6)].

Pregnancy:

Advise pregnant women of the potential risk to a fetus and/or neonate [see Use in Specific Populations (8.1)].

Lactation:

Advise women that breastfeeding is not recommended during treatment with lithium [see Use in Specific Populations (8.2)].

Distributed by:

Hikma Pharmaceuticals USA Inc.

Berkeley Heights, NJ 07922

Revised November 2022

C50000338/01

Medication Guide

Lithium (LITH-ee-əm) oral solution

Lithium Carbonate tablets

Lithium Carbonate capsules

What is the most important information I should know about Lithium and Lithium Carbonate?

Lithium and Lithium Carbonate can cause serious side effects, including:

- too much lithium in your blood (lithium toxicity). Lithium toxicity that can cause death may happen even if the lithium level in your blood is close to the right level for you. Your healthcare provider will need to monitor your blood levels of lithium to find the best dose for you. Take your Lithium or Lithium Carbonate exactly as your healthcare provider tells you to take it. Stop taking Lithium and Lithium Carbonate and call your healthcare provider right away if you have any symptoms of lithium toxicity including:

- abnormal heartbeat

- vomiting

- diarrhea

- drowsiness

- weak muscles

- blurred vision

- clumsiness

- ringing in your ears

- muscle twitching

Other symptoms may include:

- lightheadedness

- confusion

- bloating

- mood changes

- slurred speech

- breathing problems

- seizure

- coma

What is Lithium and Lithium Carbonate?

Lithium and Lithium Carbonate are prescription medicines called mood-stabilizing agents used alone (monotherapy) for:

- the acute (short-term) treatment of people 7 years of age and older with manic and mixed episodes that happen with bipolar I disorder.
- maintenance treatment of bipolar I disorder in people 7 years of age and older.

It is not known if Lithium and Lithium Carbonate are safe and effective in children under 7 years of age with bipolar I disorder.

Who should not take Lithium or Lithium Carbonate?

Do not take Lithium or Lithium Carbonate if you are allergic to Lithium or any of the ingredients in Lithium Carbonate or Lithium Citrate. See the end of this Medication Guide for a complete list of ingredients in Lithium and Lithium Carbonate.

What should I tell my healthcare provider before taking Lithium or Lithium Carbonate?

Before taking Lithium or Lithium Carbonate, tell your healthcare provider if you:

- have kidney problems

- have heart problems

- have breathing problems

- have thyroid problems

- are pregnant or plan to become pregnant. Lithium and Lithium Carbonate may harm your
  unborn baby.

- are breastfeeding or plan to breastfeed. Lithium and Lithium Carbonate can pass into your breastmilk and may harm your baby. You should not breastfeed during treatment with Lithium or Lithium Carbonate. Talk to your healthcare provider about the best way to feed your baby if you take Lithium or Lithium Carbonate.

Tell your healthcare provider about all the medicines you take, including prescription, over-the-counter medicines, vitamins, and herbal supplements.

Using Lithium and Lithium Carbonate with certain other medicines may affect each other causing possible side effects. Lithium and Lithium Carbonate may affect the way other medicines work, and other medicines may affect how Lithium and Lithium Carbonate works.

Especially tell your healthcare provider if you take:

- MAOIs

- selective serotonin reuptake inhibitors (SSRIs)

- serotonin norepinephrine reuptake inhibitors (SNRIs)

- medicines used to treat migraine headaches called triptans

- tricyclic antidepressants

- fentanyl

- antipsychotic medicines

- tramadol

- tryptophan

- buspirone

- St. John’s Wort

Your healthcare provider can tell you if it is safe to take Lithium or Lithium Carbonate with your other medicines. Do not start or stop any medicines while taking Lithium or Lithium Carbonate without talking to your healthcare provider first.

Know the medicines you take. Keep a list of your medicines to show your healthcare provider and pharmacist when you get a new medicine.

How should I take Lithium and Lithium Carbonate?

- Take your Lithium and Lithium Carbonate exactly as prescribed by your healthcare provider.

- Your healthcare provider will do certain blood tests before starting and during treatment with Lithium and Lithium Carbonate.

- Your healthcare provider may change your dose if needed. Do not change your dose on your own.

- Do not double your dose if a dose is missed. Talk with your healthcare provider if you miss a dose.

- Do not stop taking Lithium or Lithium Carbonate suddenly without talking to your healthcare provider.

- Your healthcare provider may change your Lithium or Lithium Carbonate dose to make sure you are taking the dose that is right for you.

- If you take too much Lithium or Lithium Carbonate, call your healthcare provider or poison control center, or go to the nearest hospital emergency room right away. In case of poisoning, call your poison control center at 1-800-222-1222.

What should I avoid while taking Lithium or Lithium Carbonate?

- Do not drive, operate heavy machinery, or do other dangerous activities when you start taking Lithium or Lithium Carbonate, when your dose is changed, or until you know how Lithium or Lithium Carbonate affects you. Lithium or Lithium Carbonate can make you sleepy. Talk to your healthcare provider about these activities.

- Avoid becoming overheated or dehydrated during exercise and in hot weather. Follow your healthcare provider instructions about the type and amount of liquids you should drink. In some cases, drinking too much liquid can be as unsafe as not drinking enough.

- Do not change the amount of salt in your diet. Changing the amount of salt in your diet could change the amount of Lithium or Lithium Carbonate in your blood.

What are the possible side effects of Lithium and Lithium Carbonate?

See “What is the most important information I should know about Lithium and Lithium Carbonate?”

Lithium and Lithium Carbonate may cause serious side effects, including:

- kidney problems. People who take Lithium or Lithium Carbonate may have to urinate often (polyuria) and have other kidney problems that may affect how their kidneys work. These problems can happen within a few weeks of starting to take Lithium or Lithium Carbonate or after taking Lithium or Lithium Carbonate for a long time.

- low levels of sodium (salt) in your blood (hyponatremia). Lithium and Lithium Carbonate can cause you to lose sodium. Talk to your healthcare provider about your diet and how much fluid you are drinking when starting Lithium or Lithium Carbonate. If you have been sweating more than usual or have had diarrhea, you may need extra salt and more fluids. Talk to your healthcare provider if this happens.

- neurological problems. People who take Lithium or Lithium Carbonate with certain other medicines called antipsychotics may have symptoms such as weakness, tiredness, fever, tremors, and confusion. Talk to your healthcare provider if this happens. Ask if you are not sure about the medicines you take.

- serotonin syndrome. A potentially life-threatening problem called serotonin syndrome can happen when you take Lithium or Lithium Carbonate while you take certain medicines called serotonergic and MAOIs. Symptoms of serotonin syndrome include:

- agitation

- seeing things that are not there

- confusion

- coma

- rapid pulse

- high or low blood pressure

- dizziness

- sweating

- flushing

- fever

- tremors

- stiff muscles

- muscle twitching

- become unstable

- seizures

- nausea

- vomiting

- diarrhea

- thyroid problems.

- high calcium levels in your blood (hypercalcemia) and changes in your parathyroid gland (hyperparathyroidism) that may not go away when you stop taking Lithium or Lithium Carbonate.

- heart problems. People who take Lithium or Lithium Carbonate may find out they also have a heart problem called Brugada Syndrome. People who have unexplained fainting or who have a family history of sudden unexplained death before 45 years of age may have Brugada Syndrome and not know it. If you faint or feel abnormal heartbeats, talk to your healthcare provider right away.

- increased pressure in the brain and swelling in the eye (pseudotumor cerebri) that can cause vision problems or blindness. If you have severe headaches behind your eyes, ringing in the ears, blurred vision, double vision, or brief periods of blindness, talk to your health care provider right away.

The most common side effects of Lithium and Lithium Carbonate, include:

- Adults with manic or mixed episodes of bipolar I disorder:

- hand trembling

- excessive urination

- increased thirst

- nausea

- general discomfort when you start treatment

- Children 7 to 17 years of age with manic or mixed episodes of bipolar I disorder:

- excessive urination

- thyroid problems

- hand trembling

- excessive thirst

- dizziness

- rash

- difficulty walking

- decreased appetite

- blurred vision

- nausea

- vomiting

These are not all the possible side effects of Lithium and Lithium Carbonate.

Call your doctor for medical advice about side effects. You may report side effects to FDA at 1-800-FDA-1088.

How should I store Lithium and Lithium Carbonate?

Store Lithium and Lithium Carbonate at room temperature, between 68°F to 77°F (20°C to 25°C).

Keep capsules and tablets dry and keep in a tightly closed container.

Keep Lithium, Lithium Carbonate, and all medicines out of the reach of children.

General information about the safe and effective use of Lithium and Lithium Carbonate.

Medicines are sometimes prescribed for purposes other than those listed in a Medication Guide. Do not use Lithium or Lithium Carbonate for a condition for which it was not prescribed. Do not give Lithium or Lithium Carbonate to other people, even if they have the same symptoms you have. It may harm them. You can ask your pharmacist or healthcare provider for information about Lithium or Lithium Carbonate that is written for healthcare professionals.

For more information about Lithium and Lithium Carbonate, please call West-Ward Pharmaceuticals Corp. at 1-800-962-8364.

What are the ingredients in Lithium and Lithium Carbonate?

Active ingredient: lithium carbonate, USP (tablets and capsules) and lithium citrate (oral solution).

Inactive ingredients:

Tablets: calcium stearate, microcrystalline cellulose, povidone, purified water, sodium lauryl sulfate, and sodium starch glycolate.

Capsules: talc. The capsule shells contain black monogramming ink, FD&C Red No. 40 (300 mg and 600 mg only), gelatin and titanium dioxide. The black monogramming ink contains ammonium hydroxide, ethanol, iron oxide black, isopropyl alcohol, N-butyl alcohol, propylene glycol and shellac glaze.

Oral solution: alcohol 0.3%, citric acid, purified water, raspberry blend, sodium benzoate and sorbitol solution.

Distributed by: Hikma Pharmaceuticals USA Inc., Berkeley Heights, NJ 07922

This Medication Guide has been approved by the U.S. Food and Drug Administration.

Revised November 2022

C50000338/01

PACKAGE/LABEL PRINCIPAL DISPLAY PANEL

Lithium Oral Solution USP, 8mEq per 5mL

NDC 0054-3527-63

PACKAGE/LABEL PRINCIPAL DISPLAY PANEL

Lithium Carbonate Tablets USP, 300 mg

NDC 0054-4527-25

PACKAGE/LABEL PRINCIPAL DISPLAY PANEL

Lithium Carbonate Tablet USP, 300 mg

10 x 10 Unit-Dose

NDC 0054-8528-25

PACKAGE/LABEL PRINCIPAL DISPLAY PANEL

Lithium Carbonate Capsules USP, 150 mg

NDC 0054-2526-25

PACKAGE/LABEL PRINCIPAL DISPLAY PANEL

Lithium Carbonate Capsules, 150 mg

10 x 10 Unit Dose

NDC 0054-8526-25

PACKAGE/LABEL PRINCIPAL DISPLAY PANEL

Lithium Carbonate Capsules USP, 300 mg

NDC 0054-2527-25

PACKAGE/LABEL PRINCIPAL DISPLAY PANEL

Lithium Carbonate Capsules USP, 300 mg

10 x 10 Unit Dose

NDC 0054-8527-25

PACKAGE/LABEL PRINCIPAL DISPLAY PANEL

Lithium Carbonate Capsules USP, 600 mg

NDC 0054-2531-25

PACKAGE/LABEL PRINCIPAL DISPLAY PANEL

Lithium Carbonate Capsules USP, 600 mg

10 x 10 Unit Dose

NDC 0054-8531-25